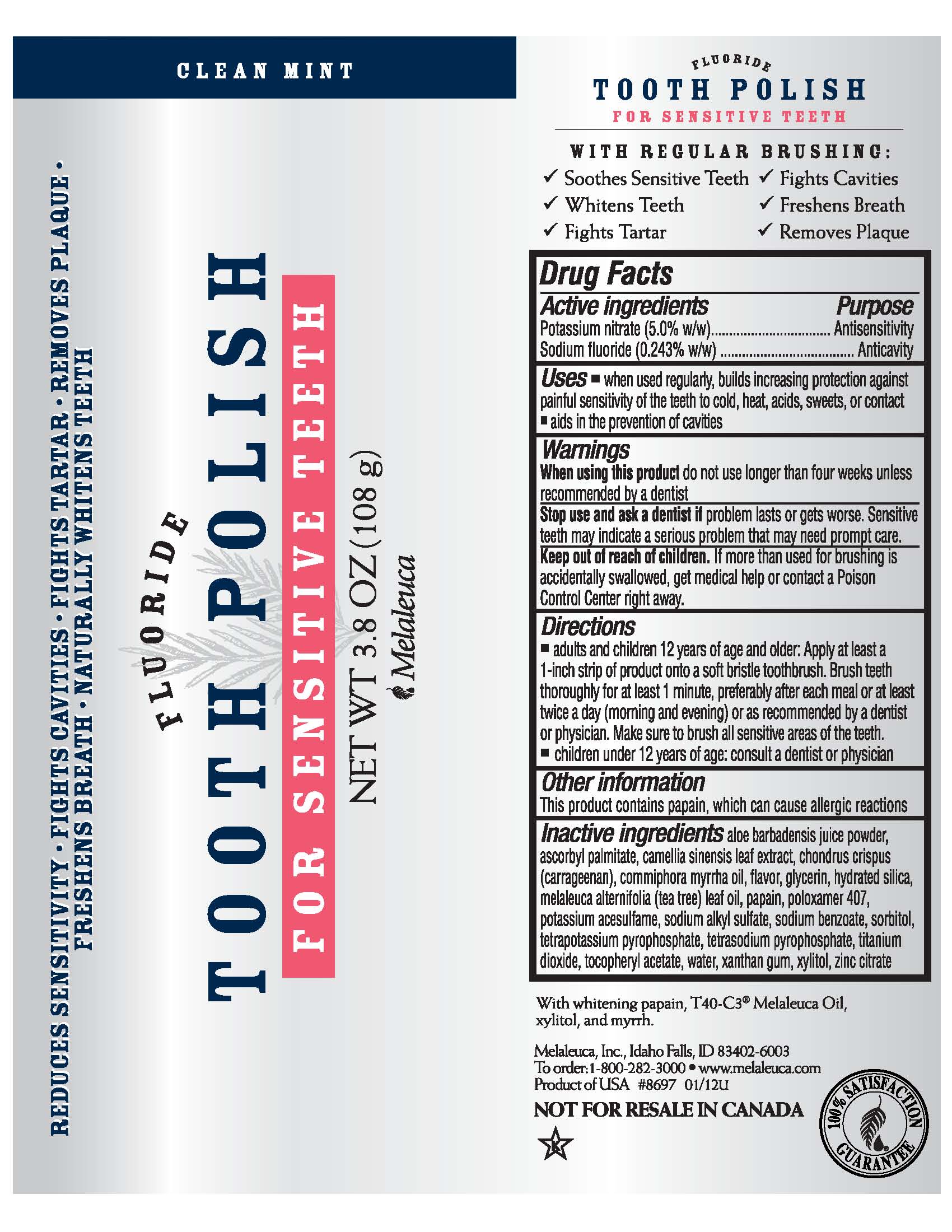 DRUG LABEL: Sensitive
NDC: 54473-302 | Form: PASTE, DENTIFRICE
Manufacturer: Melaleuca, Inc.
Category: otc | Type: HUMAN OTC DRUG LABEL
Date: 20180329

ACTIVE INGREDIENTS: SODIUM FLUORIDE 0.26244 g/108 g; POTASSIUM NITRATE 5.4 g/108 g
INACTIVE INGREDIENTS: ACESULFAME POTASSIUM; ALOE VERA LEAF; ALPHA-TOCOPHEROL ACETATE; ASCORBYL PALMITATE; CARRAGEENAN; GLYCERIN; GREEN TEA LEAF; HYDRATED SILICA; MYRRH OIL; PAPAIN; POLOXAMER 407; POTASSIUM PYROPHOSPHATE; SODIUM BENZOATE; SODIUM LAURYL SULFATE; SODIUM PYROPHOSPHATE; SORBITOL; TEA TREE OIL; TITANIUM DIOXIDE; WATER; XANTHAN GUM; XYLITOL; ZINC CITRATE

Sensitive Fluoride Tooth Polish

Active ingredients
Potassium nitrate (5.0% w/w)
Sodium fluoride (0.243% w/w)

Purpose
Antisensitivity
Anticavity

Uses

- when used regularly, builds increasing protection against painful sensitivity of the teeth to cold, heat, acids, sweets, or contact
- aids in the prevention of cavities

Warnings
When using this product do not use longer than four weeks unless recommended by a dentist

Stop use and ask a dentist if problem lasts or gets worse. Sensitive teeth may indicate a serious problem that may need prompt care.

Keep out of reach of children. If more than used for brushing is accidentally swallowed, get medical help or contact a Poison Control Center right away.

Directions

- adults and children 12 years of age and older: Apply at least a 1-inch strip of product onto a soft bristle toothbrush. Brush teeth thoroughly for at least 1 minute, preferably after each meal or at least twice a day (morning and evening) or as recommended by a dentist or physician. Make sure to brush all sensitive areas of the teeth.
- children under 12 years of age: consult a dentist or physician

Other information

This product contains papain, which may cause allergic reactions

INACTIVE INGREDIENT

Inactive ingredients aloe barbadensis juice powder, ascorbyl palmitate, camellia sinensis leaf extract, chondurs crispus (carrageenan), commiphora myrrha oil, flavor, glycerin, hydrated sisica, melaleuca alternifolia (tea tree) leaf oil, papain, poloxamer 407, potassium acesulfame, sodium alkyl sulfate, sodium benzoate, sorbitol, tetrapotassium pyrophosphate, tetrasodium pyrphosphate, titanium dioxide, tocopheryl acetate, water, xanthan gum, xylitol, zinc citrate